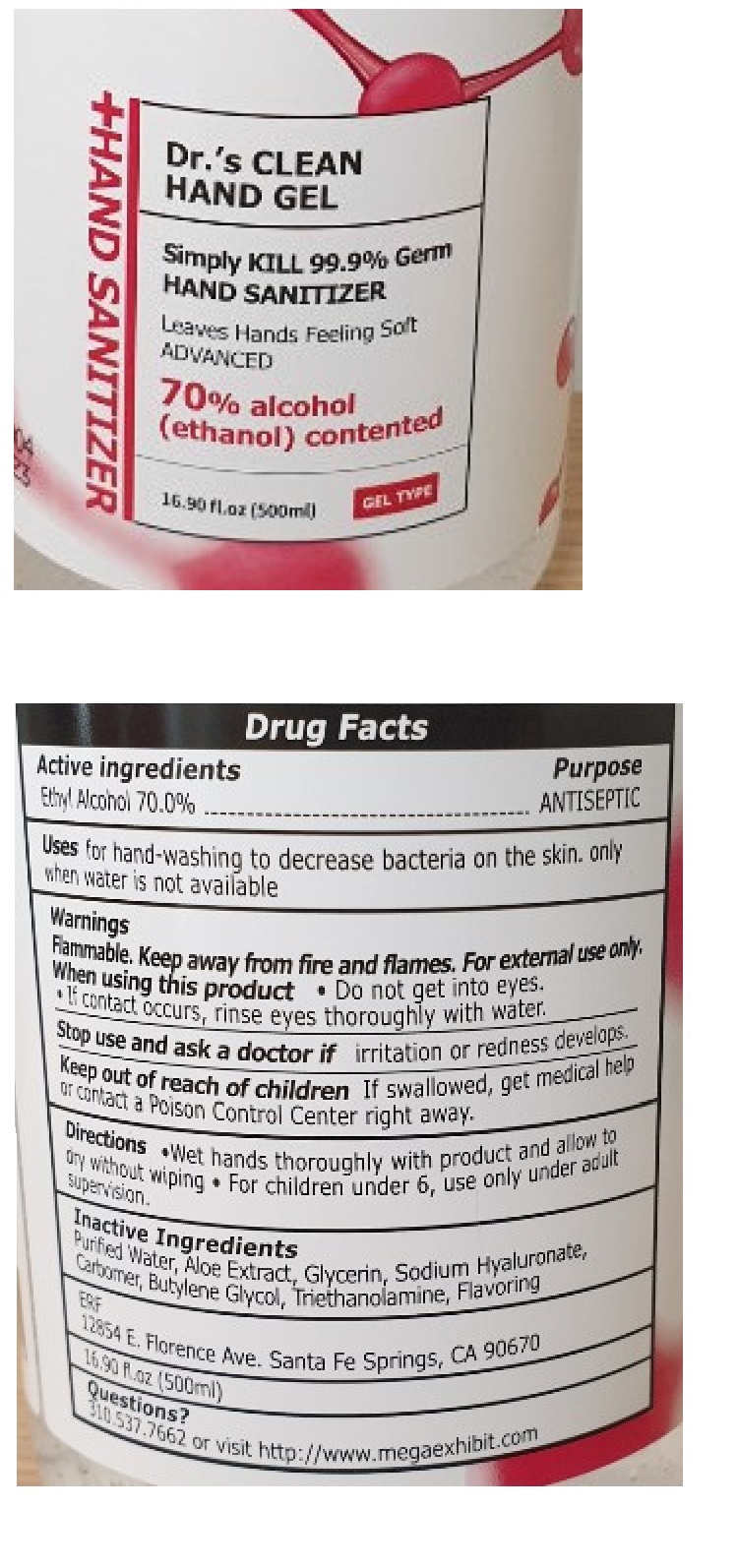 DRUG LABEL: Dr.s CLEAN HAND SANITIZER
NDC: 76724-001 | Form: GEL
Manufacturer: Erf Exhibit Inc
Category: otc | Type: HUMAN OTC DRUG LABEL
Date: 20200505

ACTIVE INGREDIENTS: ALCOHOL 70 mL/100 mL
INACTIVE INGREDIENTS: WATER; ALOE; GLYCERIN; HYALURONATE SODIUM; CARBOMER HOMOPOLYMER, UNSPECIFIED TYPE; BUTYLENE GLYCOL; TROLAMINE

Dr.s CLEAN HAND SANITIZER

Active ingredients

Ethyl Alcohol 70.0%

Purpose

ANTISEPTIC

Uses

for hand-washing to decrease bacteria on the skin. only when water is not available

Warnings

Flammable. Keep away from fire and flames. For external use only.

When using this product • Do not get into eyes.

• If contact occurs, rinse eyes thoroughly with water.

Stop use and ask a doctor ifirritation or redness develops.

Keep out of reach of children If swallowed, get medical help or contact a Poison Control Center right away.

Directions

• Wet hands thoroughly with product and allow to dry without wiping.

• For children under 6, use only under adult supervision.

Inactive Ingredients

Purified Water, Aloe Extract, Glycerin, Sodium Hyaluronate, Carbomer, Butylene Glycol, Triethanolamine, Flavoring

Questions?

310.537.7662 or visit http://www.megaexhibit.com

HAND GEL

Simply KILL 99.9% Germ

Leaves Hands Feeling Soft

ADVANCED

(ethanol) contented

ERF

12854 E. Florence Ave. Santa Fe Springs, CA 90670